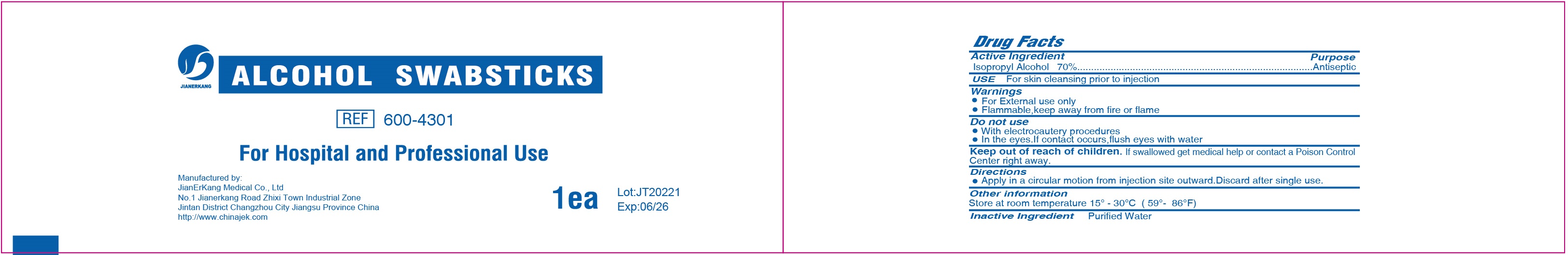 DRUG LABEL: Alcohol Swabstick
NDC: 34645-0016 | Form: SWAB
Manufacturer: Jianerkang Medical Co., Ltd
Category: otc | Type: HUMAN OTC DRUG LABEL
Date: 20231023

ACTIVE INGREDIENTS: ISOPROPYL ALCOHOL 70 mL/1 g
INACTIVE INGREDIENTS: WATER

Alcohol Swabstick

Active Ingredient

Isopropyl Alcohol 70%

Purpose

Antiseptic

USE

For skin cleansing prior to injection

Warnings

- For External use only
- Flammable, keep away from fire or flame

Do not use

- With electrocautery procedures
- In the eyes. If contact occurs, flush eyes with water

Keep out of reach of children.

If swallowed get medical help or contact a Poison Control Center right away.

Directions

- Apply in a circular motion from injection site outward. Discard after single use.

Other information

Store at room temperature 15° - 30°C (59° - 86°F)

Inactive Ingredient

Purified Water